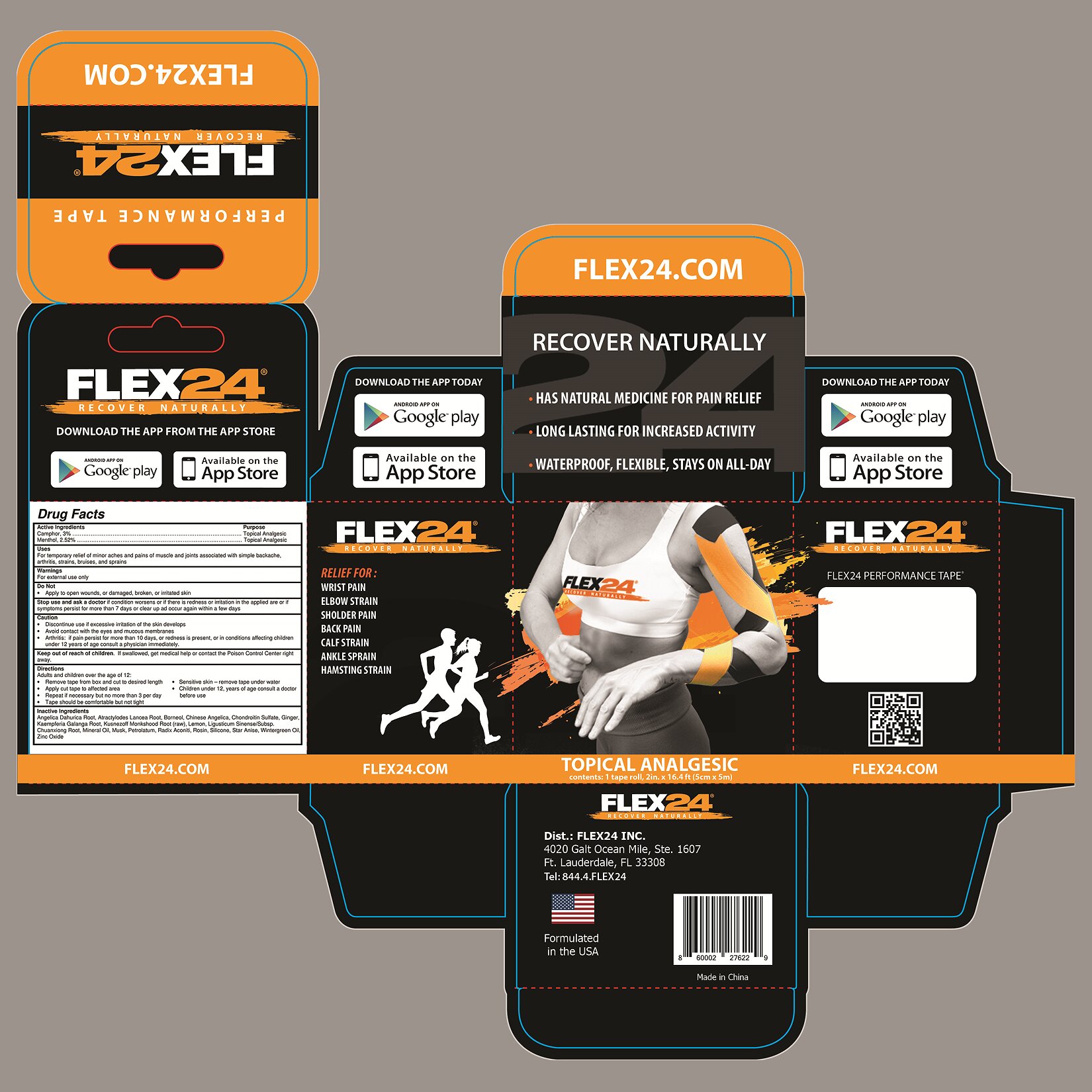 DRUG LABEL: Flex24 Tape
NDC: 73218-004 | Form: PATCH
Manufacturer: Flex24, Inc.
Category: otc | Type: HUMAN OTC DRUG LABEL
Date: 20190915

ACTIVE INGREDIENTS: CAMPHOR (NATURAL) 3 g/100 g; MENTHOL 2.52 g/100 g
INACTIVE INGREDIENTS: ANGELICA DAHURICA ROOT; ATRACTYLODES LANCEA ROOT; BORNEOL; ANGELICA SINENSIS ROOT; CHONDROITIN SULFATE (BOVINE); GINGER; KAEMPFERIA GALANGA ROOT; ACONITUM KUSNEZOFFII ROOT; LEMON; LIGUSTICUM SINENSE SUBSP. CHUANXIONG ROOT; MINERAL OIL; MOSCHUS BEREZOVSKII MUSK SAC RESIN; PETROLATUM; ACONITUM NAPELLUS ROOT; ROSIN; STAR ANISE; METHYL SALICYLATE; ZINC OXIDE

Active Ingredients

Camphor, 3%

Menthol, 2.52%

Purpose

Topical Analgesic

Uses

For the temporary relief of minor aches and pains of muscles and joints associated with simple backache, arthritis, strains, bruises, and sprains

Warnings

For external use only

Do not

- Apply to open wounds, or damaged, broken, or irritated skin

Stop use and ask a doctor

if condition worsens or if there is redness or irritation in the applied area or if symptoms persis for more than 7 days or clear up and occur again within a few days

Caution

- Discontinue use if excessive irritation of the skin develops
- Avoid contact with the eyes and mucous membranes
- Arthritis: if pain persists for more than 10 days, or redness is present, or in conditions affecting children under 12 years of age consult a physician immediately

Keep out of reach of children. If swallowed, get medical help or contact the Poison Control Center right away.

Directions

Adults and children over the age of 12:

- Remove tape from box and cut to desired length
- Apply cut tape to affected area
- Repeat if necessary but no more than 3 per day
- Tape should be comfortable but not tight
- Sensitive skin - remove tape under water

Children under 12 years of age, consult a doctor

Inactive Ingredients

Angelica Dahurica Root, atractylodes Lancea Root, Borneol, Chinese Angelica, Chondroitin Sulfate, Ginger, Kaempferia Galanga Root, Kusnezoff Monkshoot Root (raw), Lemon, Ligusticum Sinese Subsp. Chuansiong Root, Mineral Oil, Musk, Petrolatum, Radix Aconiti, Silicone, Star Anise, Wintergreen Oil, Zinc Oxide

RELIEF FOR:
WRIST PAIN
ELBOW STRAIN
SHOULDER PAIN
BACK PAIN
CALF STRAIN
ANKLE SPRAIN
HAMSTRING SPRAIN

Dist: Flex24, Inc.
4020 Galt Ocean Mile, Ste. 1607
Ft. Lauderdale, FL 33308
Tel: 844.4.FLEX24

Formulated in USA
Made in China

PACKAGE LABEL

FLEX24®
RECOVER NATURALLY

HAS NATURAL MEDICINE FOR PAIN RELIEF
LONG LASTING FOR INCREASED ACTIVITY
WATERPROOF, FLEXIBLE, STAYS ON ALL-DAY

TOPICAL ANALGESIC

contents: 1 tape roll, 2 in. x 16.4 ft. (5 cm x 5 m)